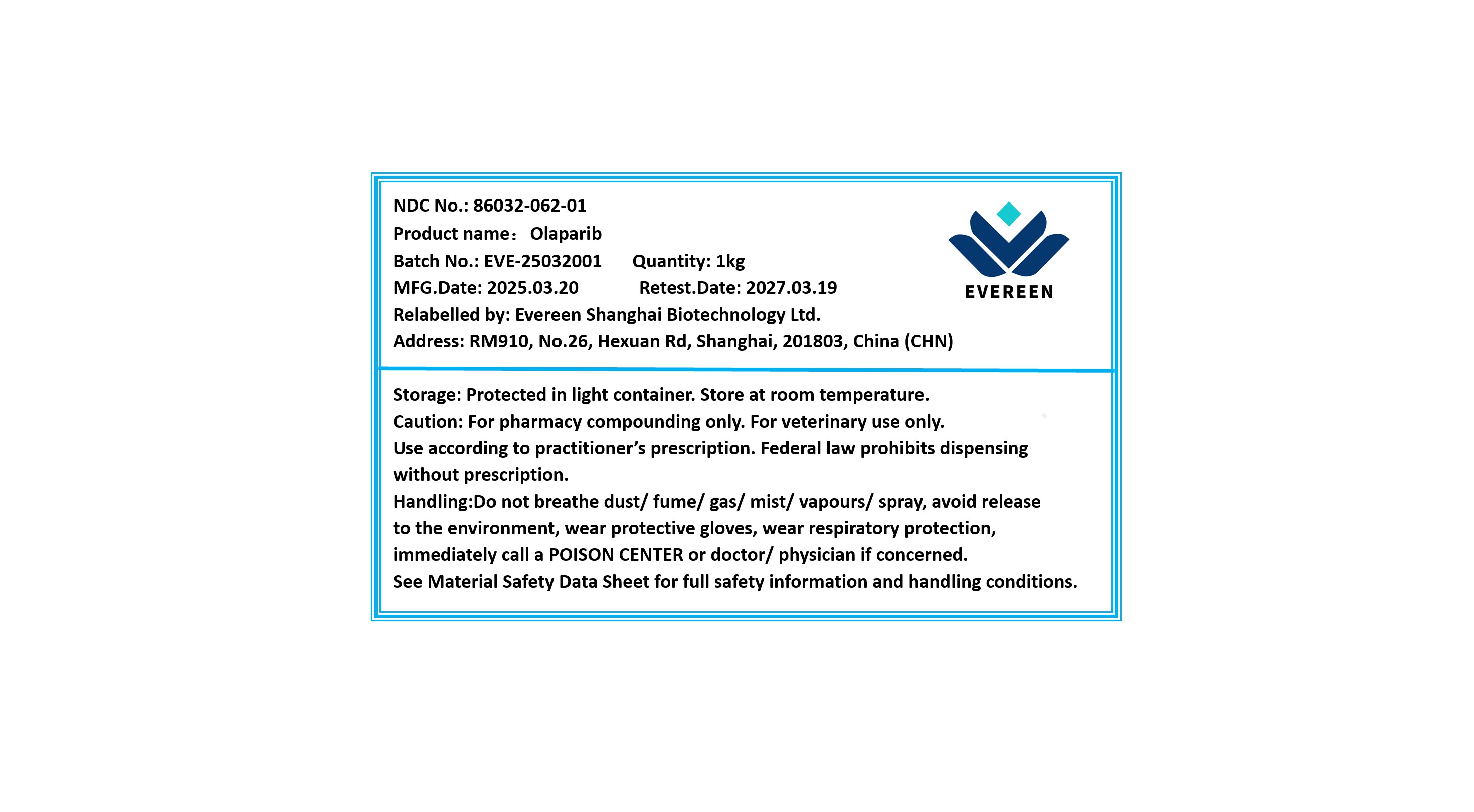 DRUG LABEL: Olaparib
NDC: 86032-062 | Form: POWDER
Manufacturer: Evereen Shanghai Biotechnology Ltd.
Category: other | Type: BULK INGREDIENT - ANIMAL DRUG
Date: 20250928

ACTIVE INGREDIENTS: OLAPARIB 1 kg/1 kg

Olaparib